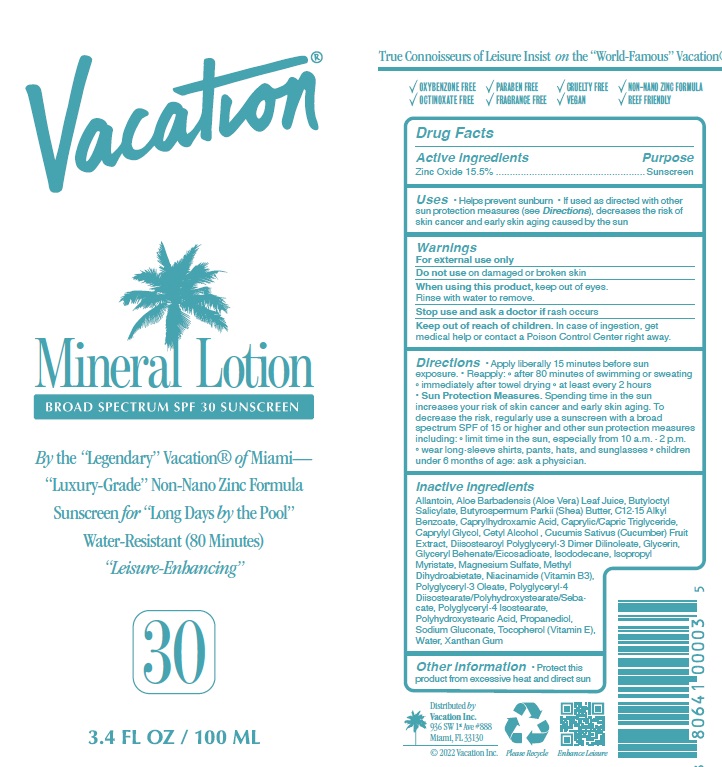 DRUG LABEL: Vacation SPF 30 Mineral
NDC: 80641-009 | Form: LOTION
Manufacturer: Vacation Inc.
Category: otc | Type: HUMAN OTC DRUG LABEL
Date: 20241220

ACTIVE INGREDIENTS: ZINC OXIDE 15.5 g/100 mL
INACTIVE INGREDIENTS: ISODODECANE; MAGNESIUM SULFATE, UNSPECIFIED; METHYL DIHYDROABIETATE; POLYGLYCERYL-4 ISOSTEARATE; PROPANEDIOL; TOCOPHEROL; XANTHAN GUM; CUCUMBER; ALLANTOIN; BUTYLOCTYL SALICYLATE; MEDIUM-CHAIN TRIGLYCERIDES; GLYCERIN; CAPRYLHYDROXAMIC ACID; SHEA BUTTER; CETYL ALCOHOL; WATER; CAPRYLYL GLYCOL; ALOE VERA LEAF; ALKYL (C12-15) BENZOATE; DIISOSTEAROYL POLYGLYCERYL-3 DIMER DILINOLEATE; GLYCERYL BEHENATE/EICOSADIOATE; ISOPROPYL MYRISTATE; NIACINAMIDE; POLYHYDROXYSTEARIC ACID (2300 MW); POLYGLYCERYL-4 DIISOSTEARATE/POLYHYDROXYSTEARATE/SEBACATE; POLYGLYCERYL-3 OLEATE; SODIUM GLUCONATE

Vacation - SPF 30 Mineral Lotion

ACTIVE INGREDIENT

Zinc Oxide 15.5%

PURPOSE

Sunscreen

Uses

• Helps prevent sunburn

• If used as directed with other sun protection measures (see Directions), decreases the risk of skin cancer and early skin aging caused by the sun

WARNINGS

For external use only
Do not use on damaged or broken skin
When using this product, keep out of eyes. Rinse with water to remove.
Stop use and ask a doctor if rash occurs

Keep out of reach of children. In case of ingestion, get medical help or contact a Poison Control Center right away.

Directions

• Apply liberally 15 minutes before sun exposure.

• Reapply: after 80 minutes of swimming or sweating, immediately after towel drying, at least every 2 hours
• Sun Protection Measures. Spending time in the sun increases your risk of skin cancer and early skin aging. To decrease the risk, regularly use a sunscreen with a broad spectrum SPF of 15 or higher and other sun protection measures including: limit time in the sun, especially from 10 a.m. - 2 p.m. wear long-sleeve shirts, pants, hats, and

INACTIVE INGREDIENT

Allantoin, Aloe Barbadensis (Aloe Vera) Leaf Juice, Butyloctyl Salicylate, Butyrospermum Parkii (Shea) Butter, C12-15 Alkyl Benzoate, Caprylhydroxamic Acid, Caprylic/Capric Triglyceride, Caprylyl Glycol, Cetyl Alcohol , Cucumis Sativus (Cucumber) Fruit Extract, Diisostearoyl Polyglyceryl-3 Dimer Dilinoleate, Glycerin, Glyceryl Behenate/Eicosadioate, Isododecane, Isopropyl Myristate, Magnesium Sulfate, Methyl Dihydroabietate, Niacinamide (Vitamin B3), Polyglyceryl-3 Oleate, Polyglyceryl-4 Diisostearate/Polyhydroxystearate/Sebacate, Polyglyceryl-4 Isostearate, Polyhydroxystearic Acid, Propanediol, Sodium Gluconate, Tocopherol (Vitamin E), Water, Xanthan Gum

Other Information

• Protect this product from excessive heat and direct sun